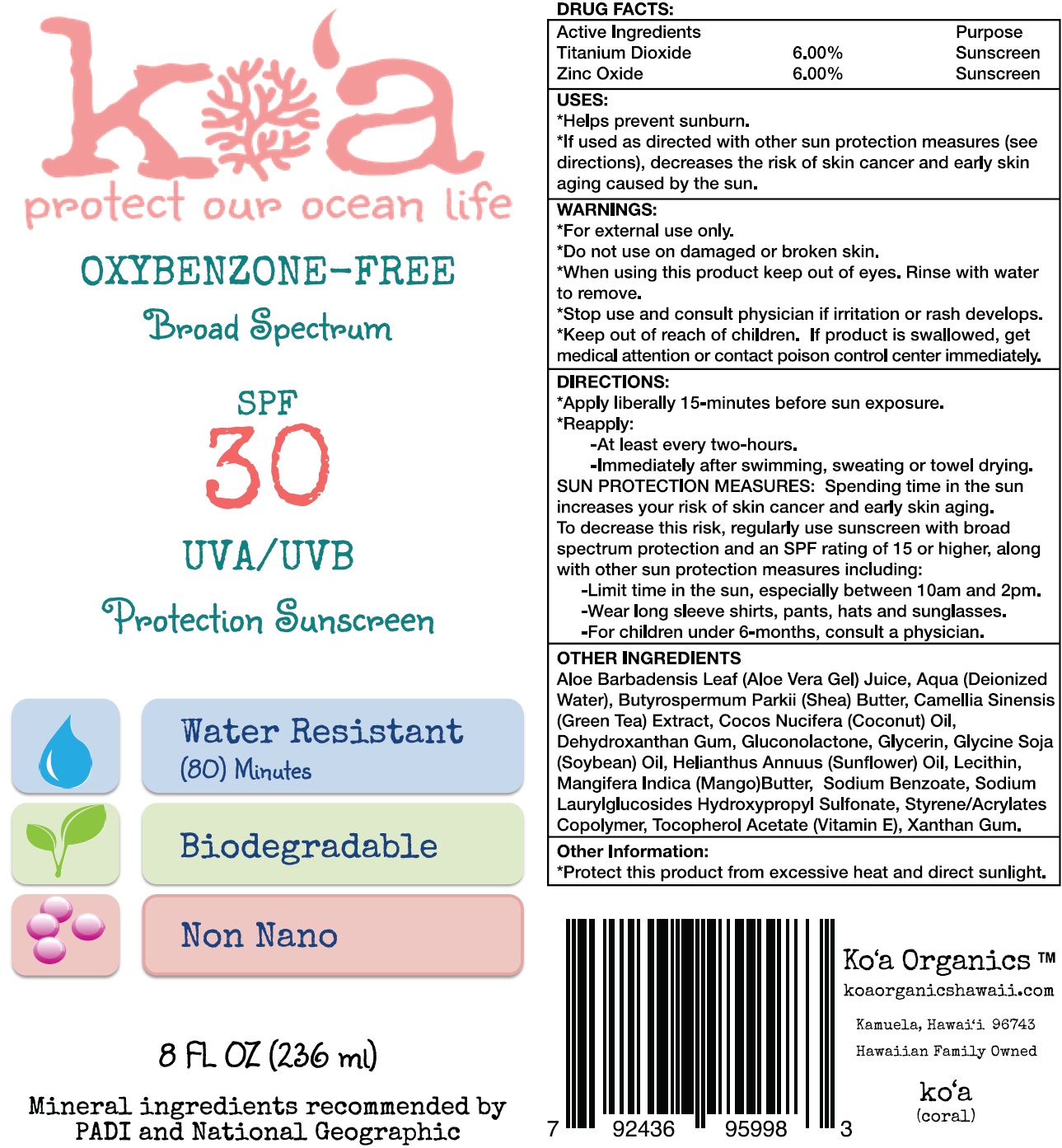 DRUG LABEL: koa protect our ocean life OXYBENZONE FREE Broad Spectrum SPF 30 UVA UVB Protection Sunscreen
NDC: 71889-350 | Form: CREAM
Manufacturer: Kapa'ihi, Inc
Category: otc | Type: HUMAN OTC DRUG LABEL
Date: 20231111

ACTIVE INGREDIENTS: TITANIUM DIOXIDE 60 mg/1 mL; ZINC OXIDE 60 mg/1 mL
INACTIVE INGREDIENTS: ALOE VERA LEAF; WATER; SHEA BUTTER; GREEN TEA LEAF; COCONUT OIL; DEHYDROXANTHAN GUM; GLUCONOLACTONE; GLYCERIN; SOYBEAN OIL; HELIANTHUS ANNUUS FLOWERING TOP; MANGIFERA INDICA SEED BUTTER; SODIUM BENZOATE; .ALPHA.-TOCOPHEROL ACETATE; XANTHAN GUM

koa protect our ocean life OXYBENZONE-FREE Broad Spectrum SPF 30 UVA/UVB Protection Sunscreen

Active Ingredients

Titanium Dioxide (6.00%)

Zinc Oxide (6.00%)

Purpose

Sunscreen

USES:

Helps prevent sunburn. If used as directed with other sun protection measures (see directions) decreases the risk of skin cancer and early skin aging caused by the sun.

WARNINGS:

For external use only.

Do not use

on damaged or broken skin.

When using this product

keep out of eyes. Rinse with water to remove.

Stop use and consult physician

if irritation or rash develops.

Keep out of reach of children.

If product is swallowed, get medical attention or contact poison control center immediately

DIRECTIONS:

Apply liberally 15-minutes before sun exposure. Reapply at least every two-hours or immediately after swimming. sweating or towel drying. SUN PROTECTION MEASURES, Spending time in the sun increases your risk of skin cancer and early skin aging. To decrease this risk, regularly use sunscreen with broad spectrum protection and an SPF rating of 15 or higher, along with other sun protection measures including: - Wear long sleeve shirts, pants, hats and sunglasses. - For children under 6-months, consult a physician.

OTHER INGREDIENTS

Aloe Barbadensis Leaf (Aloe Vera Gel) Juice, Aqua (Deionized Water), Butyrospermum Parkii (Shea) Butter, Camellia Sinensis (Green Tea) Extract, Cocos Nucifera (Coconut) Oil, Dehydroxanthan Gum, Gluconolactone, Glycerin, Glycine Soja (Soybean) Oil, Helianthus Annuus (Sunflower) Oil, Lecithin, Mangifera Indica (Mango) Seed Butter. Sodium Benzoate, Sodium Laurylglucosides Hydroxypropyl Sulfonate, Styrene/Acrylates Copolymer, Tocopherol Acetate (Vitamin E), Xanthan Gum.

Other Information:

Protect this product from excessive heat and direct sunlight